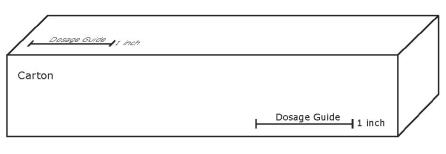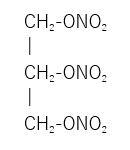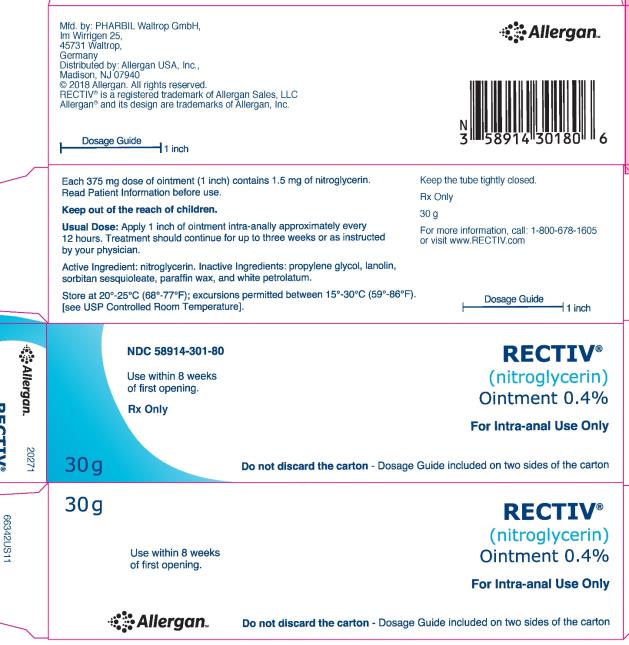 DRUG LABEL: Rectiv
NDC: 58914-301 | Form: OINTMENT
Manufacturer: Allergan, Inc.
Category: prescription | Type: HUMAN PRESCRIPTION DRUG LABEL
Date: 20240729

ACTIVE INGREDIENTS: NITROGLYCERIN 4 mg/1 g
INACTIVE INGREDIENTS: PROPYLENE GLYCOL; LANOLIN; SORBITAN SESQUIOLEATE; PARAFFIN; WHITE PETROLATUM

HIGHLIGHTS OF PRESCRIBING INFORMATION

These highlights do not include all the information needed to use RECTIV® safely and effectively. See full prescribing information for RECTIV.
RECTIV (nitroglycerin) Ointment 0.4%, for intra-anal use
Initial U.S. Approval: 1955

1 INDICATIONS AND USAGE

RECTIV is a nitrate vasodilator indicated for the treatment of moderate to severe pain associated with chronic anal fissure (1).

2 DOSAGE AND ADMINISTRATION

Apply 1 inch of ointment (375 mg of ointment equivalent to 1.5 mg of nitroglycerin) intra-anally every 12 hours for up to 3 weeks (2).

RECTIV ointment is not for oral, ophthalmic, or intravaginal use (2)

3 DOSAGE FORMS AND STRENGTHS

Ointment 0.4% w/w (4 mg nitroglycerin/1 g ointment) (3)

4 CONTRAINDICATIONS

- Use of PDE5 inhibitors (e.g. sildenafil, vardenafil and tadalafil) as these are shown to potentiate the hypotensive effects of organic nitrates. (4.1).
- Severe anemia (4.2)
- Increased intracranial pressure (4.3)
- Known hypersensitivity to nitroglycerin, other nitrates and nitrites, or any components of the ointment. (4.4)

5 WARNINGS AND PRECAUTIONS

- Cardiovascular Disorders: Venous and arterial dilatation as a consequence of nitroglycerin treatment can result in hypotension. Exercise caution when treating patients with any of the following conditions: blood volume depletion, existing hypotension, cardiomyopathies, congestive heart failure, acute myocardial infarction, or poor cardiac function for other reasons (5.1).
- Headache: Nitroglycerin produces dose-related headaches which may be severe (5.2)

6 ADVERSE REACTIONS

Most common adverse reactions are headache and dizziness. (6)

To report SUSPECTED ADVERSE REACTIONS, contact AbbVie Inc. at 1-800-678-1605 or FDA at 1-800-FDA-1088 or www.fda.gov/medwatch.

7 DRUG INTERACTIONS

- PDE5 inhibitors: potentiation of hypotensive effects of organic nitrates; concomitant use is contraindicated. (4.1, 7.1)
- Antihypertensives: possible additive hypotensive effects. (7.2)
- Aspirin: increased nitroglycerin levels. (7.3)
- Tissue-type Plasminogen Activator (t-PA): decreased thrombolytic effect. (7.4)
- Heparin: anticoagulant effect of heparin may be reduced. Monitor APTT. (7.5)
- Ergotamine: increased bioavailability of ergotamine. (7.6)
- Alcohol: Additive vasodilatory effects to nitroglycerin. Consumption of alcohol should be avoided. (7.7)

FULL PRESCRIBING INFORMATION

1 INDICATIONS AND USAGE

RECTIV® (nitroglycerin) Ointment 0.4% is indicated for the treatment of moderate to severe pain associated with chronic anal fissure.

2 DOSAGE AND ADMINISTRATION

Apply 1 inch of ointment (375 mg of ointment equivalent to 1.5 mg of nitroglycerin) intra-anally every 12 hours for up to 3 weeks. A finger covering, such as plastic-wrap, disposable surgical glove or a finger cot, should be placed on the finger to apply the ointment. To obtain a 1.5 mg dose of nitroglycerin, the covered finger is laid alongside the 1 inch dosing line on the carton.

Refer to carton for accurate dosage guide.

The tube is gently squeezed until a line of ointment the length of the measuring line is expressed onto the covered finger. The ointment is gently inserted into the anal canal using the covered finger no further than to the first finger joint and the ointment is applied around the side of the anal canal. If this cannot be achieved due to pain, application of the ointment should be made directly to the outside of the anus. Treatment may be continued for up to three weeks.

RECTIV ointment is not for oral, ophthalmic, or intravaginal use. Hands should be washed after application of the ointment [see Patient Instruction].

3 DOSAGE FORMS AND STRENGTHS

Ointment, 0.4% w/w (4 mg /1 g) in 30 g tubes.

4 CONTRAINDICATIONS

4.1 PDE5 inhibitor use

Administration of RECTIV is contraindicated in patients who are using a selective inhibitor of cyclic guanosine monophosphate (cGMP)-specific phosphodiesterase type 5 (PDE5), such as sildenafil, vardenafil, and tadalafil, as these are shown to potentiate the hypotensive effects of organic nitrates [see DRUG INTERACTIONS (7.1)].

4.2 Severe anemia

RECTIV is contraindicated in patients with severe anemia.

4.3 Increased intracranial pressure

RECTIV is contraindicated in patients with increased intracranial pressure.

4.4 Hypersensitivity

RECTIV is contraindicated in patients who have shown hypersensitivity to it or to other nitrates or nitrites. Skin reactions consistent with hypersensitivity have been observed with organic nitrates.

5 WARNINGS AND PRECAUTIONS

5.1 Cardiovascular disorders

Venous and arterial dilatation as a consequence of nitroglycerin treatment including RECTIV, can decrease venous blood returning to the heart and reduce arterial vascular resistance and systolic pressure. Exercise caution when treating patients with any of the following conditions: blood volume depletion, existing hypotension, cardiomyopathies, congestive heart failure, acute myocardial infarction, or poor cardiac function for other reasons. If patients with any of these conditions are treated with RECTIV, monitor cardiovascular status and clinical condition. The adverse reactions of RECTIV are likely to be more pronounced in the elderly.

5.2 Headache

RECTIV produces dose-related headaches, which may be severe. Tolerance to headaches occurs.

6 ADVERSE REACTIONS

Because clinical trials are conducted under widely varying conditions, adverse reaction rates observed in the clinical trials of a drug cannot be directly compared to rates in the clinical trials of another drug and may not reflect the rates observed in practice.

The most common adverse reaction of RECTIV ointment applied to the anal canal is headache.

Headache may be recurrent following each dose. Headaches are typically of short duration and can be treated with an analgesic, e.g. acetaminophen, and are reversible upon discontinuation of treatment.

In Study REC-C-001, a double-blind, placebo-controlled trial in patients with a painful chronic anal fissure, the most frequent (≥ 2%) adverse reactions reported were as follows (Table 1):

Table 1: Incidence of Adverse Reactions (≥ 2%) in Study REC-C-001
 | RECTIV N = 123 |  | Placebo N = 124
System Organ Class Preferred term | Patients n (%) | Events n | Patients n (%) | Events n
Nervous system disorders
Headache | 79 (64) | 938 | 51 (41) | 225
Dizziness | 6 (5) | 26 | 0 | 0

Hypotension

Transient episodes of light-headedness, occasionally related to blood pressure changes, also may occur. Hypotension (including orthostatic hypotension) occurs infrequently, but in some patients may be severe enough to warrant discontinuation of therapy.

Allergic Reactions

Flushing, allergic reactions and application site reactions (including drug rash and exfoliative dermatitis) have been reported rarely.

Methemoglobinemia

In rare cases, therapeutic doses of organic nitrates have caused methemoglobinemia [see OVERDOSAGE (10)].

7 DRUG INTERACTIONS

7.1 PDE5 inhibitors

Phosphodiesterase type 5 (PDE5) inhibitors such as sildenafil, vardenafil, and tadalafil have been shown to potentiate the hypotensive effects of organic nitrates.

The time course of the interaction appears to be related to the half-life of the PDE5 inhibitor, however, the dose dependence of this interaction has not been studied. Use of RECTIV within a few days of PDE5 inhibitors is contraindicated.

7.2 Antihypertensives

Patients receiving antihypertensive drugs, beta-adrenergic blockers, and other nitrates should be observed for possible additive hypotensive effects when using RECTIV. Marked orthostatic hypotension has been reported when calcium channel blockers and organic nitrates were used concomitantly.

Beta-blockers blunt the reflex tachycardia produced by nitroglycerin without preventing its hypotensive effects. If beta-blockers are used with RECTIV in patients with angina pectoris, additional hypotensive effects may occur.

7.3 Aspirin

Coadministration of aspirin (at doses between 500 mg and 1000 mg) and nitroglycerin has been reported to result in increased nitroglycerin maximum concentrations by as much as 67% and AUC by 73% when administered as a single dose. The pharmacological effects of RECTIV may be enhanced by concomitant administration of aspirin.

7.4 Tissue-type Plasminogen Activator (t-PA)

Intravenous administration of nitroglycerin decreases the thrombolytic effect of tissue-type plasminogen activator (t-PA). Plasma levels of t-PA are reduced when coadministered with nitroglycerin. Therefore, caution should be observed in patients receiving RECTIV during t-PA therapy.

7.5 Heparin

Although an interaction has been reported between intravenous heparin and intravenous nitroglycerin (resulting in a decrease in the anticoagulant effect of heparin), the data are not consistent. If patients are to receive intravenous heparin and RECTIV concurrently, the anticoagulation status of the patient must be checked.

7.6 Ergotamine

Oral administration of nitroglycerin markedly decreases the first-pass metabolism of dihydroergotamine and consequently increases its oral bioavailability. Ergotamine is known to precipitate angina pectoris. Therefore the possibility of ergotism in patients receiving RECTIV should be considered.

7.7 Alcohol

The vasodilating effects of nitroglycerin have been shown to be additive to the effects observed with alcohol.

8 USE IN SPECIFIC POPULATIONS

8.1 Pregnancy

Risk Summary

There are no data on the use of nitroglycerin ointment intra-anally during pregnancy to determine a drug-associated risk of major birth defects, miscarriage or other adverse maternal or fetal outcomes. In animal reproduction studies, no malformations were observed in offspring of pregnant rats and rabbits administered nitroglycerin by topical or dietary route during the period of organogenesis (see Data).

The background risk of major birth defects and miscarriage for the indicated population is unknown. All pregnancies have a background risk of birth defect, loss, or other adverse outcomes. In the U.S. general population, the estimated background risk of major birth defects and miscarriage in clinically recognized pregnancies is 2% to 4% and 15% to 20%, respectively.

Data

Animal Data

Animal reproduction studies in rats and rabbits were conducted with topically applied nitroglycerin ointment at doses up to 80 mg/kg/day and 240 mg/kg/day, respectively. No toxic effects on dams or fetuses were seen at any dose tested.

An animal reproduction study was conducted in rats with nitroglycerin administered in the diet at levels up to 1% content (approximately 430 mg/kg/day) on days 6 to 15 of gestation. In offspring of the high-dose group, an increased but not statistically significant incidence of diaphragmatic hernias was noted together with decreased hyoid bone ossification. The latter finding probably reflects delayed development, thus indicating no clear evidence of a potential teratogenic effect of nitroglycerin.

8.2 Lactation

Risk Summary

There are no data on the presence of nitroglycerin in either human or animal milk following topical administration, or the effects of nitroglycerin on milk production. A publication describing 40 lactating patients who used nitroglycerin ointment to treat chronic anal fissures for varied durations did not report signs of adverse effects in their breastfed infants, however, the dosing regimens were not described. The developmental and health benefits of breastfeeding should be considered along with the clinical need for RECTIV and any potential adverse effects on the breastfed infant from RECTIV or from the underlying maternal condition.

8.4 Pediatric Use

The safety and effectiveness of RECTIV in pediatric patients under 18 years of age have not been established.

8.5 Geriatric Use

Clinical studies of RECTIV did not include sufficient numbers of subjects aged 65 and over to determine whether they respond differently from younger subjects. Clinical data from the published literature indicate that the elderly demonstrate increased sensitivity to nitrates, which may be therapeutic but also manifest by more frequent or severe hypotension and related dizziness or fainting. Increased sensitivity may reflect the greater frequency of decreased hepatic, renal, or cardiac function, and of concomitant disease or other drug therapy.

10 OVERDOSAGE

Nitroglycerin toxicity is generally mild. The estimated adult oral lethal dose of nitroglycerin is 200 mg to 1,200 mg. Infants may be more susceptible to toxicity from nitroglycerin. Consultation with a poison center should be considered.

Laboratory determinations of serum levels of nitroglycerin and its metabolites are not widely available, and such determinations have, in any event, no established role in the management of nitroglycerin overdose.

No data are available to suggest physiological maneuvers (e.g., maneuvers to change the pH of the urine) that might accelerate elimination of nitroglycerin and its active metabolites. Similarly, it is not known which, if any, of these substances can usefully be removed from the body by hemodialysis.

No specific antagonist to the vasodilator effects of nitroglycerin is known, and no intervention has been subject to controlled study as a therapy of nitroglycerin overdose. Because the hypotension associated with nitroglycerin overdose is the result of venodilatation and arterial hypovolemia, prudent therapy in this situation should be directed toward increase in central fluid volume. Passive elevation of the patient’s legs may be sufficient, but intravenous infusion of normal saline or similar fluid may also be necessary.

The use of epinephrine or other arterial vasoconstrictors in this setting is not recommended.

In patients with renal disease or congestive heart failure, therapy resulting in central volume expansion is not without hazard. Treatment of RECTIV overdose in these patients may be subtle and difficult, and invasive monitoring may be required.

Methemoglobinemia

Methemoglobinemia has been rarely reported with organic nitrates. The diagnosis should be suspected in patients who exhibit signs of impaired oxygen delivery despite adequate arterial PO2. Classically, methemoglobinemic blood is described as chocolate brown, without color change on exposure to air.

If methemoglobinemia is present, intravenous administration of methylene blue, 1 to 2 mg/kg of body weight, may be required.

11 DESCRIPTION

Nitroglycerin is 1,2,3,-propanetriol trinitrate, an organic nitrate whose structural formula is as follows:

and whose molecular weight is 227.09. RECTIV (nitroglycerin) Ointment 0.4% contains 0.4% nitroglycerin w/w (4 mg nitroglycerin/1 g ointment), propylene glycol, lanolin, sorbitan sesquioleate, paraffin wax, and white petrolatum. RECTIV (nitroglycerin) Ointment 0.4% is available in tubes with a one-inch dosing line on the carton allowing the measurement of approximately 375 mg of nitroglycerin ointment 0.4% (1.5 mg nitroglycerin) for application.

12 CLINICAL PHARMACOLOGY

12.1 Mechanism of Action

Nitroglycerin forms free radical nitric oxide (NO), which activates guanylate cyclase, resulting in an increase of guanosine 3’,5’-monophosphate (cyclic GMP) in smooth muscle and other tissues. This leads to dephosphorylation of myosin light chains, which regulates the contractile state in smooth muscle and results in vasodilatation.

12.2 Pharmacodynamics

The principal pharmacological action of nitroglycerin is relaxation of vascular smooth muscle. Intra-anal application of nitroglycerin reduces sphincter tone and resting intra-anal pressure.

12.3 Pharmacokinetics

Absorption: In six healthy subjects, the average absolute bioavailability of nitroglycerin applied to the anal canal as a 0.2% w/w ointment was approximately 50% of the 0.75 mg nitroglycerin dose.

Distribution: The volume of distribution of nitroglycerin following intravenous administration is about 3 L/kg. At plasma concentrations between 50 and 500 ng/mL, the binding of nitroglycerin to plasma proteins is approximately 60%, while that of 1,2- and 1,3-dinitroglycerin is 60% and 30%, respectively.

Metabolism: Nitroglycerin is metabolized by a liver reductase enzyme to glycerol di- and mononitrate metabolites and ultimately to glycerol and organic nitrate. Known sites of extrahepatic metabolism include red blood cells and vascular walls. In addition to nitroglycerin, the two major metabolites, 1,2- and 1,3- dinitroglycerols are found in plasma. The contribution of metabolites to the relaxation of the internal anal sphincter is unknown. The dinitrates are further metabolized to nonvasoactive mononitrates and ultimately to glycerol and carbon dioxide.

Elimination: Metabolism is the primary route of drug elimination. Nitroglycerin plasma concentrations decrease rapidly with a mean elimination half-life of two to three minutes. Half-life values range from 1.5 to 7.5 minutes. Clearance (13.6 L/min) greatly exceeds hepatic blood flow.

13 NONCLINICAL TOXICOLOGY

13.1 Carcinogenesis, Mutagenesis, Impairment of Fertility

Carcinogenesis

Animal carcinogenicity studies with topically applied nitroglycerin have not been performed.

Rats receiving up to 434 mg/kg/day of dietary nitroglycerin for 2 years developed dose-related fibrotic and neoplastic changes in liver, including carcinomas, and interstitial cell tumors in testes. At the highest dose, the incidence of hepatocellular carcinomas was 52% compared to 0% in untreated controls. Incidence of testicular tumors were 52% vs. 8% in controls. Lifetime dietary administration of up to 1058 mg/kg/day of nitroglycerin was not tumorigenic in mice.

Mutagenesis

Nitroglycerin was mutagenic in the in vitro bacterial reverse mutation (Ames) assay with Salmonella typhimurium. A similar mutation in this S. typhimurium was also reported with other NO donors. There was no evidence of clastogenic potential in multiple assays including a rodent dominant lethal assay, an in vitro Chinese Hamster Ovary assay that was conducted in the absence of metabolic activation, and several in vivo chromosomal aberration assays conducted in rats and dogs.

Impairment of Fertility

In a three-generation reproduction study, rats received dietary nitroglycerin at doses up to approximately 434 mg/kg/day for 6 months prior to mating of the F0 generation with treatment continuing through successive F1 and F2 generations. The high dose was associated with decreased feed intake and body weight gain in both sexes at all matings. No specific effect on the fertility of the F0 generation was seen. Infertility noted in subsequent generations, however, was attributed to increased interstitial cell tissue and aspermatogenesis in the high-dose males.

14 CLINICAL STUDIES

RECTIV ointment was evaluated in a 3-week double-blind, randomized, multi-center, placebo-controlled study. Patients with a painful chronic anal fissure for at least 6 weeks and moderate or severe pain prior to treatment (≥ 50 mm on the 100mm visual analog scale, VAS) were randomized to receive 0.4% (1.5mg) nitroglycerin or placebo ointment applied to the anal canal every 12 hours. Pain as assessed by the change in VAS from baseline to Days 14-18 was lower in patients receiving 0.4% ointment compared to placebo. The mean change from baseline was 44mm for RECTIV and 37mm for placebo. The difference in the mean change in pain between RECTIV and placebo was
-7.0mm (95% Confidence Interval: -13.6 to -0.4mm).

16 HOW SUPPLIED/STORAGE AND HANDLING

RECTIV (nitroglycerin) Ointment 0.4% is available in 30 g (NDC 58914-301-80) aluminum tubes with polyethylene screw caps.

Store at 20°-25°C (68°-77°F); excursions permitted between 15°-30°C (59°-86°F). [See USP Controlled Room Temperature].

Keep the tube tightly closed. Use within 8 weeks of first opening.

17 PATIENT COUNSELING INFORMATION

Advise the patient to read the FDA-approved patient labeling (Patient Information and Instructions for Use).

Interaction with PDE5 inhibitors

Advise patient not to use RECTIV with medications for erectile dysfunction such as Viagra (sildenafil), Levitra (vardenafil), and Cialis (tadalafil). These products have been shown to increase the hypotensive effects of RECTIV and other nitrate drugs [see Contraindications (4)].

Hypotension

Advise patients that treatment with RECTIV may be associated with light-headedness on standing, especially just after rising from a lying or seated position. The effect may be more frequent in patients who have also consumed alcohol, since alcohol use contributes to hypotension. Advise patients to stand up from the supine or sitting position slowly.

Headaches

Advise patients that headaches sometimes accompany treatment with RECTIV. For patients who get these headaches, the headaches may indicate the activity of the drug. Tolerance to headaches develops. Advise patients that if they experience headache they should not alter the schedule of their RECTIV treatment to avoid the occurrence of headache. An analgesic, such as acetaminophen, may be used to prevent or relieve the headaches.

Dizziness

Advise patients that dizziness has been reported as a side-effect of treatment with RECTIV.

Advise patients not to drive or operate machinery immediately after applying RECTIV.

Manufactured by:
PHARBIL Waltrop-GmbH
Im Wirrigen 25
45731 Waltrop
Germany

Distributed by:
AbbVie Inc.
North Chicago, IL 60064

© 2024 AbbVie. All rights reserved.
RECTIV and its design are trademarks of Allergan Sales, LLC, an AbbVie company.

Patient Information

RECTIV® [REC-tiv]

(Nitroglycerin) Ointment 0.4%

IMPORTANT: For intra-anal use only

Read the Patient Information that comes with RECTIV before you start using the product and each time you get a refill because there may be new information. This information does not take the place of talking to your healthcare provider about your medical condition or your treatment. If you have any questions about RECTIV, ask your healthcare provider.

What is RECTIV?

RECTIV is a prescription medicine used to treat moderate to severe pain caused by chronic anal fissures. An anal fissure is a tear in the skin lining the anal canal.

RECTIV is not suitable for children and adolescents under the age of 18 years because it has not been assessed in people in this age group.

Who should not use RECTIV?

Do not use RECTIV if you:

- are taking a medicine for erectile dysfunction (male impotence), for example Viagra (sildenafil), Cialis (tadalafil) or Levitra (vardenafil).
- have been told by your doctor that you have severe anemia (low numbers of red blood cells in your blood)
- have increased intracranial pressure or high pressure within your skull e.g. following head trauma or bleeding in your brain
- are allergic to any of the ingredients in RECTIV or if you have had allergic reactions to similar medicines in the past. See the end of this leaflet for a list of ingredients in RECTIV.

What should I tell my healthcare provider before using RECTIV?

Tell your healthcare provider about all your medical conditions, including if you:

- have low blood pressure
- have recently had a heart attack
- have heart or blood vessel disorders
- suffer from migraine or recurrent headaches
- are pregnant or plan to become pregnant. It is not known if RECTIV will harm your unborn baby.
- are breast-feeding or plan to breast-feed. It is not known if the components of RECTIV will harm your child if you breast-feed.

RECTIV may lower your blood pressure. When getting up from a lying or sitting position, you should get up slowly, otherwise you might feel faint.

Tell your healthcare provider about all the medicines you take, including prescription and non-prescription medicines, vitamins and herbal supplements. Other medicines may affect how RECTIV works. RECTIV may also affect how other medicines work.

Specifically, tell your doctor if you are taking any of the following:

- other nitroglycerin containing products
- a medicine for erectile dysfunction (male impotence), for example sildenafil, tadalafil or vardenafil (see the section above ‘Who should not use RECTIV’)
- medicines used to treat high blood pressure
- are taking aspirin, ergotamine (used to treat migraine) or are receiving tissue-type plasminogen activator (used to help dissolve blood clots formed in blood vessels in the heart, lungs and brain)
- are to be given heparin. If so, close monitoring of your blood will be required as your dose of heparin may need to be altered. Please discuss with your doctor before stopping RECTIV.

How should RECTIV be used?

Use RECTIV exactly as prescribed. See detailed Patient Instructions for Applying RECTIV at the end of this Patient Information leaflet.

Treatment may be continued for up to 3 weeks. If your anal pain does not get better after using RECTIV you should talk to your doctor.

What should I avoid while using RECTIV?

Do not drive or operate machinery immediately after applying RECTIV. If you feel dizzy or light-headed after applying the ointment do not drive or operate machinery until the dizziness has stopped.

Avoid consuming alcohol while you are being treated with RECTIV as your blood pressure is more likely to be affected if you consume alcoholic beverages.

What are the possible side effects of RECTIV?

RECTIV can cause serious side-effects: Stop using the ointment and seek medical attention immediately if you have an allergic reaction. You may have swelling of the face, lips, tongue or throat, or difficulty breathing.

Common side-effects of RECTIV are:

- Headaches, which can be severe. You could take painkillers for this (such as acetaminophen). If the headaches are unpleasant, you may need to ask your doctor whether you should stop using RECTIV.
- Dizziness, faintness on standing, or light-headedness

These are not all the possible side effects of RECTIV. Tell your healthcare provider if you have any side effect that bothers you or that does not go away. For more information, ask your healthcare provider or pharmacist.

Call your doctor for medical advice about side effects. You may report side effects to FDA at 1-800-FDA-1088.

How should I store RECTIV?

- Store at 20°-25°C (68°-77°F); excursions permitted between 15°-30°C (59°-86°F). [See USP Controlled Room Temperature].
- Keep the tube tightly closed.
- Use within 8 weeks of first opening.

Keep RECTIV out of the reach of children.

Do not use RECTIV after the expiry date which is stated on the label and carton after ‘EXP.’ The expiry date refers to the last day of that month.

General information about RECTIV

Medicines are sometimes prescribed for conditions that are not mentioned in Patient Information leaflets. Do not use RECTIV for a condition for which it is not prescribed. Do not give RECTIV to other people, even if they have the same symptoms you have. It may harm them.

This Patient Information leaflet summarizes the most important information about RECTIV. If you would like more information, talk to your healthcare provider. You can ask your pharmacist or healthcare provider for information about RECTIV that is written for health professionals.

For more information call 1-800-678-1605 or visit www.RECTIV.com.

Patient Instructions for Use

When do I apply the ointment?

Apply the ointment every 12 hours exactly as your doctor has told you to.

How do I apply the ointment?

Cover your finger with plastic-wrap, a disposable surgical glove or a finger cot.

Lay the covered finger alongside the 1 inch dosing line marked on the side of the medicine box (see figure below) so that the tip of your finger is at one end of the dosing line. Starting at the tip of the finger, squeeze the ointment onto your finger for the same length marked on the box.

Refer to carton for accurate dosage guide.

Gently insert the finger with the ointment into the anal canal, up to the first finger joint. Carefully smear the ointment around the inner sides of the anal canal. If this cannot be achieved due to pain, application of the ointment should be made directly to the outside of the anus.

What do I do after I have applied the ointment?

Throw away the finger covering in the garbage, out of the reach of children and pets. Wash your hands.

What are the ingredients in RECTIV?

Active ingredient: nitroglycerin

Inactive ingredients: propylene glycol, lanolin, sorbitan sesquioleate, paraffin wax and white petrolatum.

Manufactured by:
PHARBIL Waltrop GmbH
Im Wirrigen 25
45731 Waltrop
Germany

Distributed by:
AbbVie Inc.
North Chicago, IL 60064

© 2024 AbbVie. All rights reserved.

RECTIV and its design are trademarks of Allergan Sales, LLC, an AbbVie company.

PRINCIPAL DISPLAY PANEL

NDC 58914-301-80
RECTIV®
(nitroglycerin)
Ointment 0.4%
For Intra-anal Use only
Do not discard the carton – Dosage Guide included on two sides of the carton
30 g
Use within 8 weeks of first opening.
Rx Only